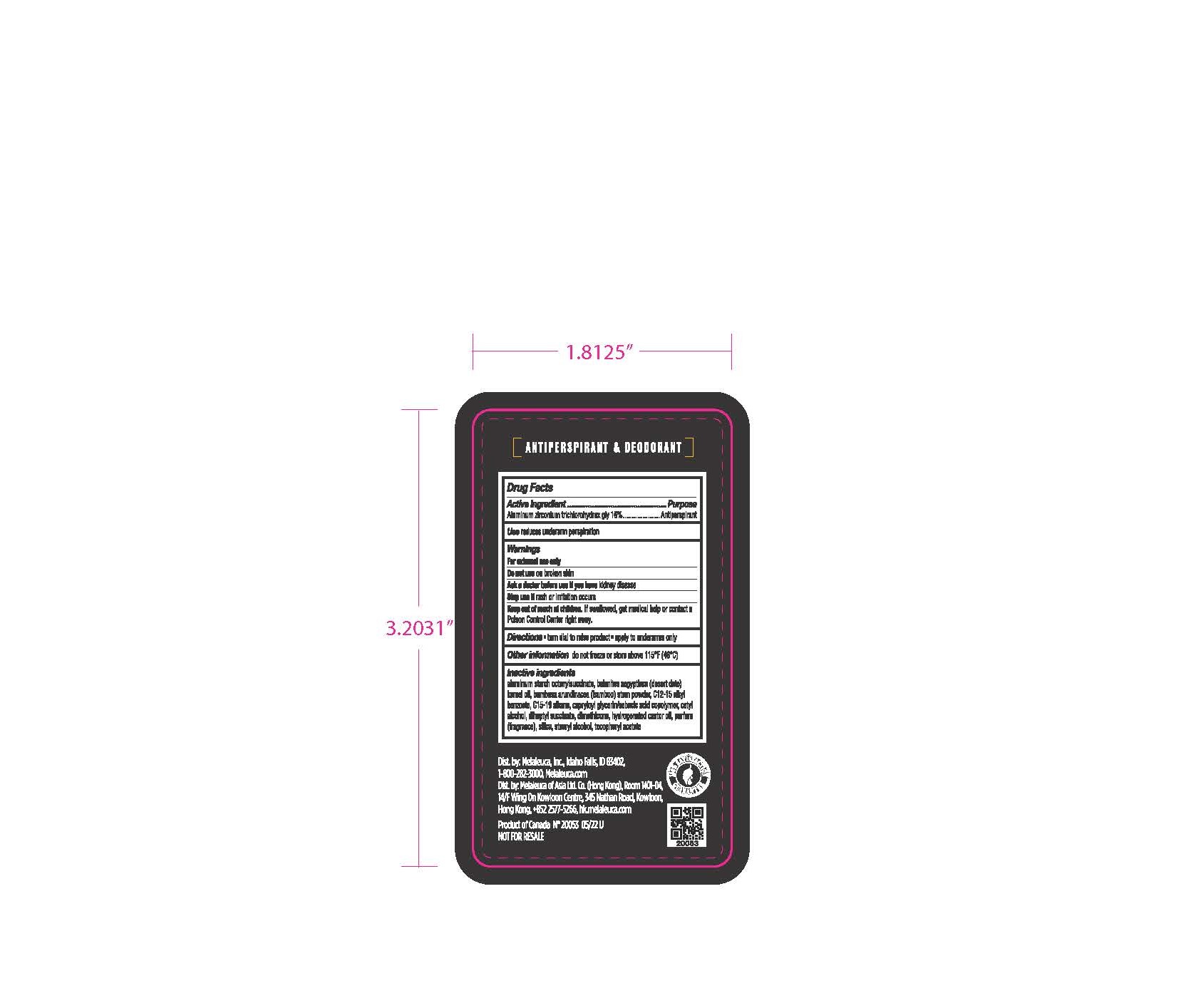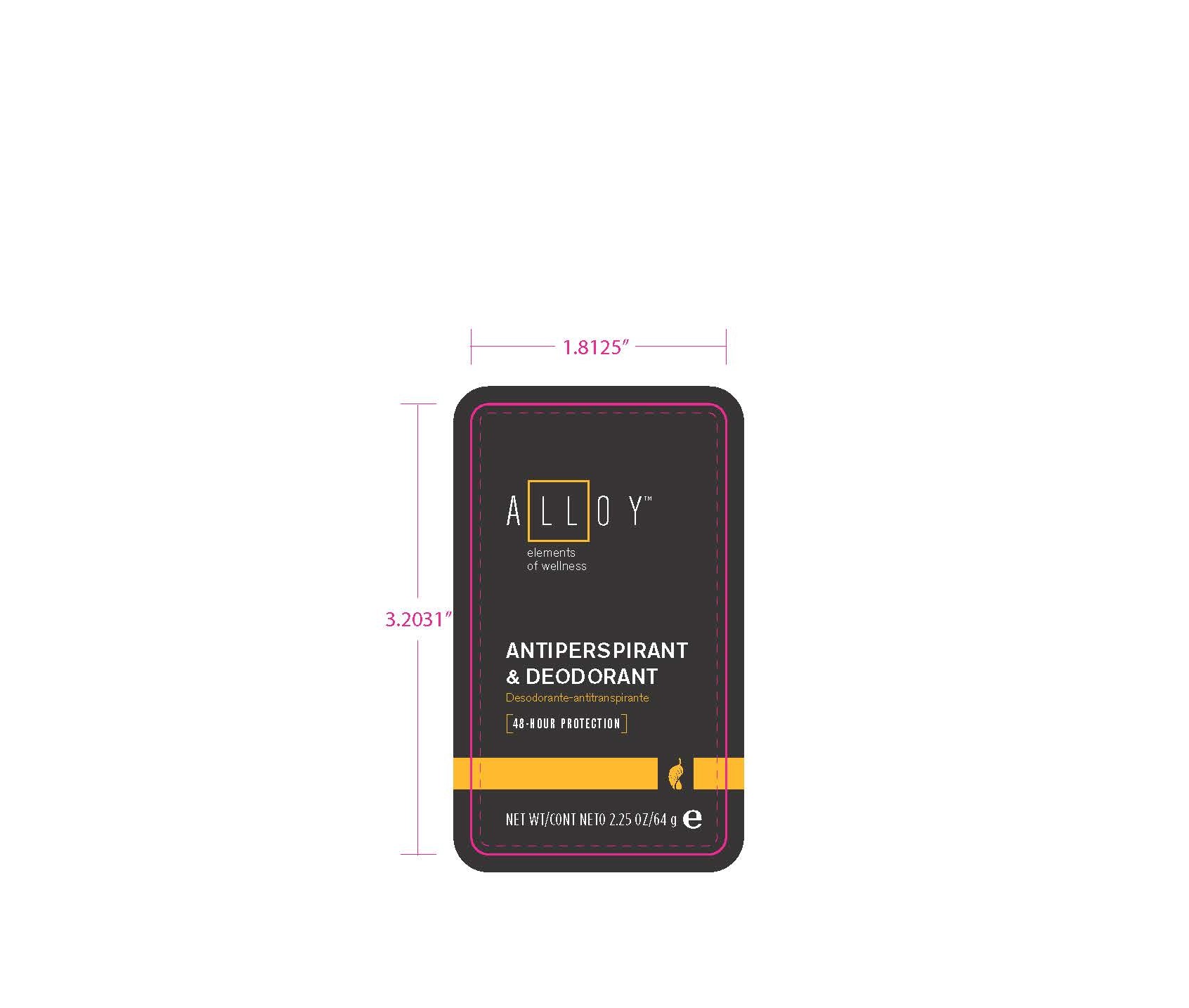 DRUG LABEL: Alloy Antiperspirant and Deodorant
NDC: 54473-339 | Form: STICK
Manufacturer: Melaleuca, Inc
Category: otc | Type: HUMAN OTC DRUG LABEL
Date: 20250214

ACTIVE INGREDIENTS: ALUMINUM ZIRCONIUM TRICHLOROHYDREX GLY 10.24 g/64 g
INACTIVE INGREDIENTS: .ALPHA.-TOCOPHEROL ACETATE; ALUMINUM STARCH OCTENYLSUCCINATE; ALKYL (C12-15) BENZOATE; SILICON DIOXIDE; BAMBUSA ARUNDINACEA STEM; DIMETHICONE; STEARYL ALCOHOL; C15-19 ALKANE; DIHEPTYL SUCCINATE; WATER; HYDROGENATED CASTOR OIL; CETYL ALCOHOL; CAPRYLOYL GLYCERIN/SEBACIC ACID COPOLYMER (2000 MPA.S); BALANITES AEGYPTIACA SEED OIL

Alloy Antiperspirant & Deodorant